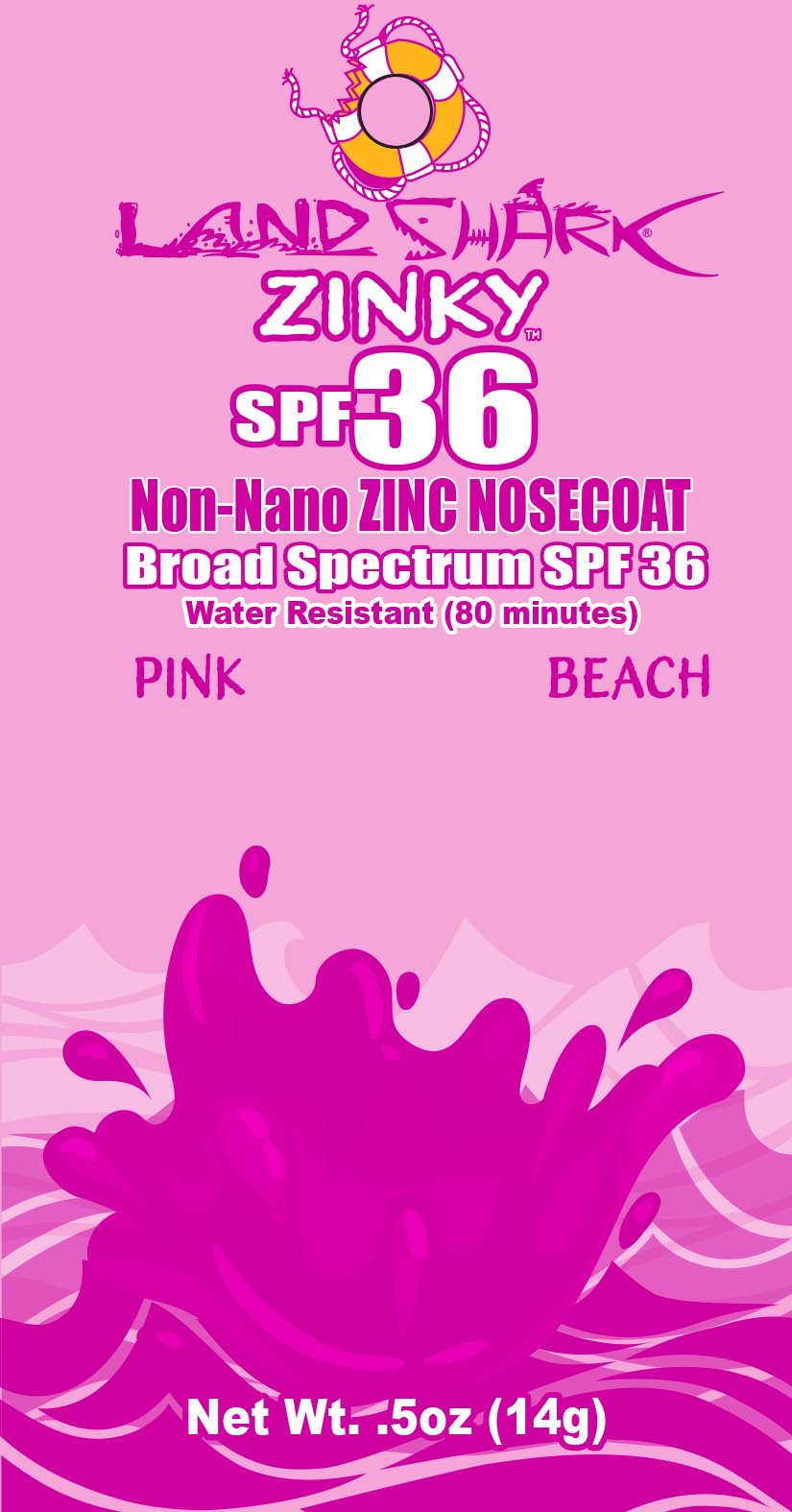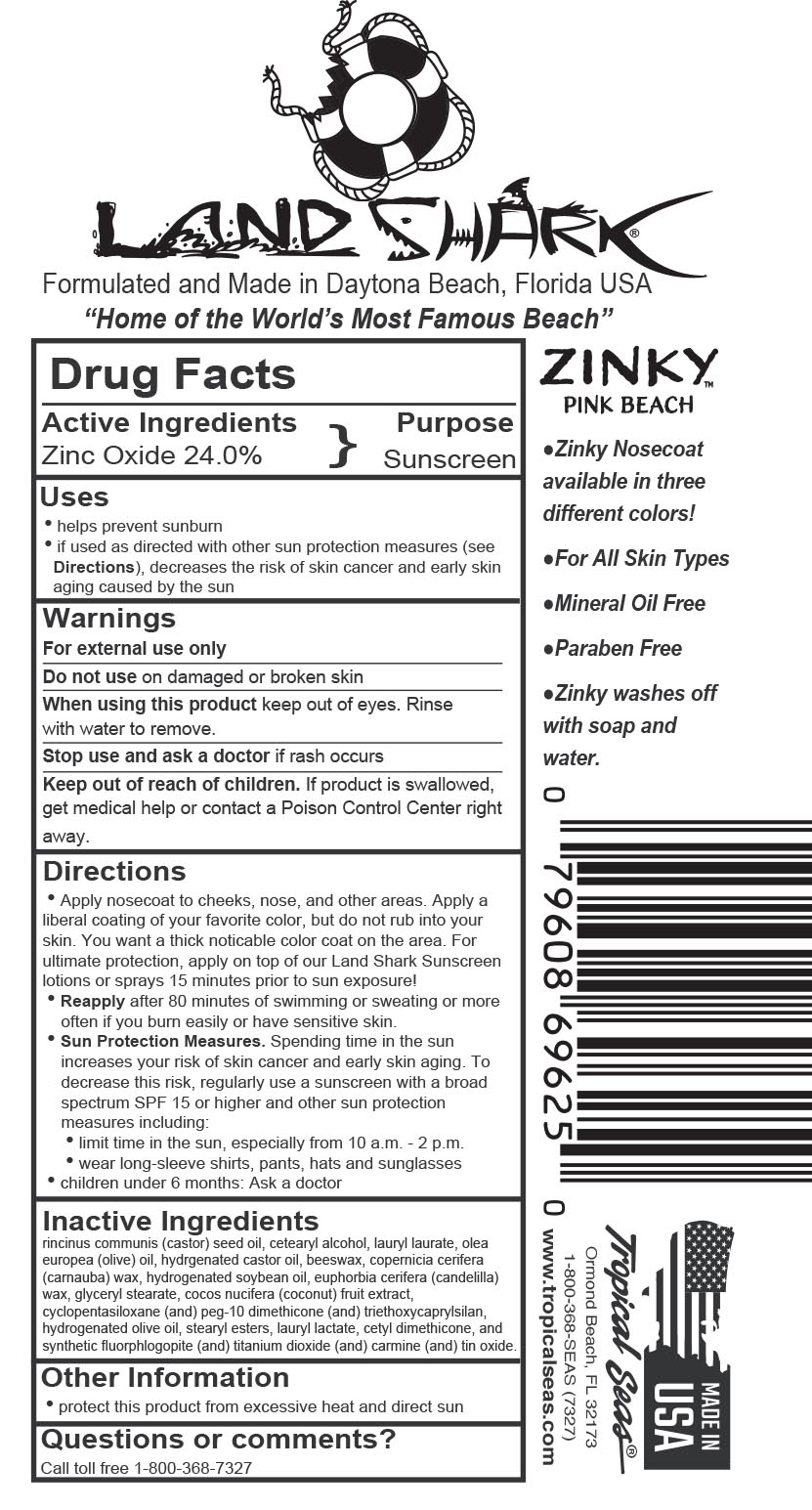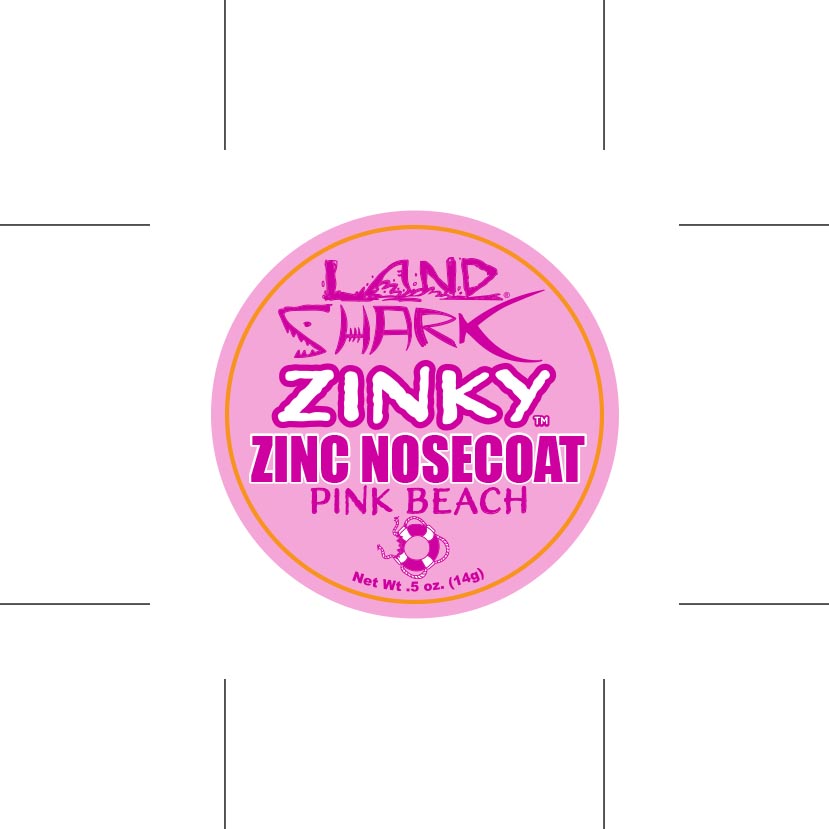 DRUG LABEL: Land Shark Zinky SPF 36 Pink Beach
NDC: 52854-625 | Form: CREAM
Manufacturer: Tropical Seas, Inc.
Category: otc | Type: HUMAN OTC DRUG LABEL
Date: 20251104

ACTIVE INGREDIENTS: ZINC OXIDE 24 g/100 g
INACTIVE INGREDIENTS: PIGMENT RED 5; STANNIC OXIDE; HYDROGENATED OLIVE OIL; CYCLOMETHICONE 5; PEG-10 DIMETHICONE (600 CST); CANDELILLA WAX; CASTOR OIL; CETOSTEARYL ALCOHOL; LAURYL LAURATE; OLIVE OIL; HYDROGENATED CASTOR OIL; YELLOW WAX; CARNAUBA WAX; HYDROGENATED SOYBEAN OIL; GLYCERYL STEARATE SE; COCONUT; CETYL DIMETHICONE 150; HIPPOPHAE RHAMNOIDES SEED OIL; HYDROGENATED OLIVE OIL STEARYL ESTERS; TRIETHOXYCAPRYLYLSILANE; LAURYL LACTATE; TITANIUM DIOXIDE; MAGNESIUM POTASSIUM ALUMINOSILICATE FLUORIDE

Land Shark Zinky Pink Beach

Drug Facts

Active Ingredients

Zinc Oxide 24.0%

Purpose

Sunscreen

Uses

- helps prevent sunburn
- if used as directed with other sun protection measures (see Directions), decreases the risk of skin cancer and early skin aging caused by the sun

Warnings

For external use only *Keep out of eyes

Stop use and ask a doctor if rash occurs

Keep out of reach of children.

Directions

- Apply nosecoat to cheeks, nose, and other areas. Apply a liberal coating of your favorite color, but do not rub into your skin. You want a thick noticable color coat on the area. For ultimate protection, apply on top of our Land Shark Sunscreen lotions or sprays 15 minutes prior to sun exposure!
- Reapply after 80 minutes of swimming or sweating or more often if you burn easily or have sensitive skin.
- Sun Protection Measures. Spending time in the sun increases your risk of skin cancer and early skin aging. To decrease this risk, regularly use a sunscreen with a broad spectrum 15 or higher and other sun protection measures including:
- limit time in the sun, especially from 10 a.m. - 2 p.m.
- wear long-sleeve shirts, pants, hats, and sunglasses
- children under 6 months: Ask a doctor

Inactive Ingredients

ricinus communis (castor) seed oil, cetearyl alcohol, lauryl laurate, olea europaea (olive) oil, hydrogenated castor oil, beeswax, copernicia cerifera (carnauba) wax, flavor, hydrogenated soybean oil, euphorbia cerifera (candelilla) wax, glyceryl stearate, cocos nucifera (coconut) fruit extract, cyclopentasiloxane (and) peg-10 dimethicone (and) triethoxycaprylsilan, hydrogenated olive oil, stearyl esters, lauryl lactate, cetyl dimethicone, and synthetic fluorphlogopite (and) titanium dioxide (and) carmine (and) tin oxide.

Principal Display Panel - Label

14g NDC 52854-615-01 Jar Label

14g NDC 52854-615-01 Blister Card Front

14g NDC 52854-615-01 Blister Card Back